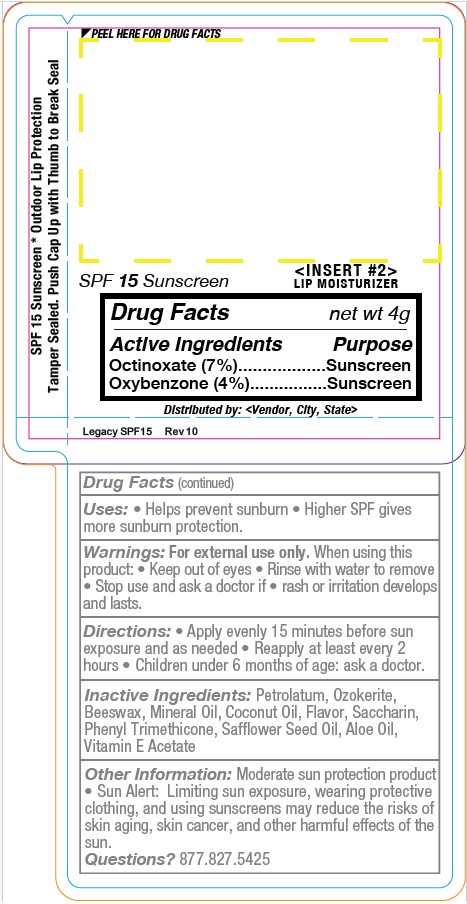 DRUG LABEL: YMLABS
NDC: 10827-0004 | Form: STICK
Manufacturer: Yusef Manufacturing Laboratories
Category: otc | Type: HUMAN OTC DRUG LABEL
Date: 20260112

ACTIVE INGREDIENTS: OXYBENZONE 0.168 g/4.2 g; OCTINOXATE 0.294 g/4.2 g
INACTIVE INGREDIENTS: LIGHT MINERAL OIL; CERESIN; WHITE WAX; MINERAL OIL; COCONUT OIL; SACCHARIN CALCIUM; PHENYL TRIMETHICONE; SAFFLOWER OIL; ALOE; ALPHA-TOCOPHEROL ACETATE

YMlabs SPF15 Flavored Lip Balm

SPF 15Sunscreen

LIP MOISTURIZER

Drug Factsnet wt 4.2g
Active Ingredients Purpose
Octinoxate (7%).............Sunscreen
Oxybenzone (4%)...........Sunscreen

Made in the USA

Distributed by
<Vendor, City, ST>

Drug Facts(continued)
Uses: • Helps prevent sunburn • Higher SPF gives
more sunburn protection.

Warnings: For external use only.When using this
product: • Keep out of eyes • Rinse with water to remove
• Stop use and ask a doctor if rash or irritation develops
and lasts.

INSTRUCTIONS FOR USE

Directions:• Apply evenly 15 minutes before sun
exposure and as needed • Reapply at least every 2
hours • Children under 6 months of age: ask a doctor.

Inactive Ingredients:Petrolatum, Ozokerite,
Beeswax, Mineral Oil, Coconut Oil, Flavor, Saccharin,
Phenyl Trimethicone, Safflower Seed Oil, Aloe Oil,
Vitamin E Acetate

Other Information:Moderate sun protection product
• Sun Alert: Limiting sun exposure, wearing protective
clothing, and using sunscreens may reduce the risks of
skin aging, skin cancer, and other harmful effects of the
sun.
Questions?877.827.5425